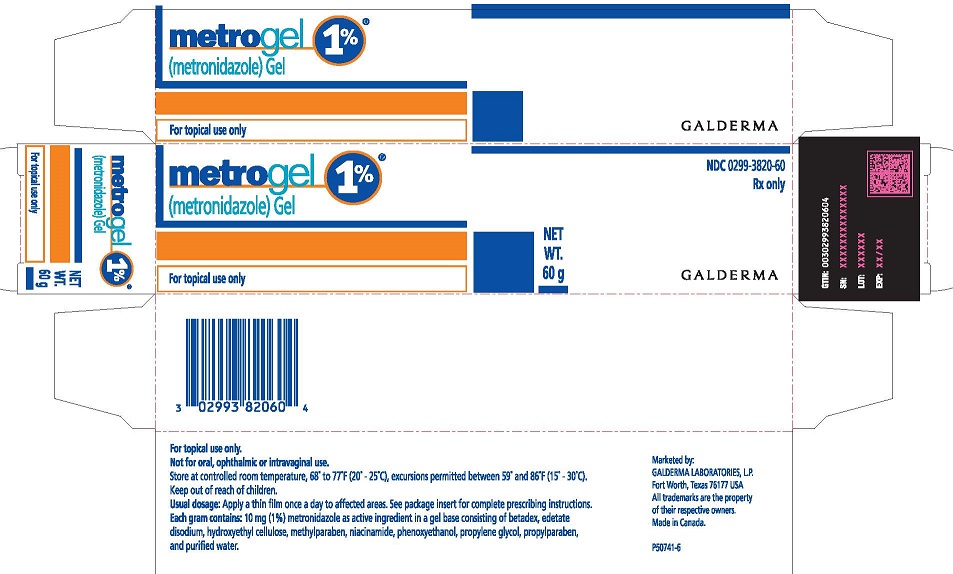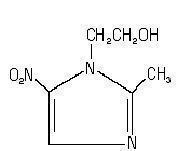 DRUG LABEL: METROGEL
NDC: 0299-3820 | Form: GEL
Manufacturer: Galderma Laboratories, L.P.
Category: prescription | Type: HUMAN PRESCRIPTION DRUG LABEL
Date: 20231127

ACTIVE INGREDIENTS: METRONIDAZOLE 10 mg/1 g
INACTIVE INGREDIENTS: betadex; edetate disodium; methylparaben; niacinamide; phenoxyethanol; propylene glycol; propylparaben; water

HIGHLIGHTS OF PRESCRIBING INFORMATION

These highlights do not include all the information needed to use METROGEL, 1% safely and effectively. See full prescribing information for METROGEL, 1%
METROGEL® (metronidazole) topical gel
Initial U.S. Approval 1963

1 INDICATIONS AND USAGE

METROGEL, 1% is a nitroimidazole indicated for the topical treatment of inflammatory lesions of rosacea. (1)

2 DOSAGE AND ADMINISTRATION

- Cleanse treated areas before the application of METROGEL. (2)
- Apply and rub in a thin film of METROGEL once daily to affected area(s). (2)
- Cosmetics may be applied after the application of METROGEL. (2)
- Not for oral, ophthalmic, or intravaginal use. (2)

3 DOSAGE FORMS AND STRENGTHS

Gel, 1%

4 CONTRAINDICATIONS

METROGEL is contraindicated in those patients with a history of hypersensitivity to metronidazole or to any other ingredient in this formulation. (4)

5 WARNINGS AND PRECAUTIONS

- Neurologic Disease: Peripheral neuropathy, characterized by numbness or paresthesia of an extremity has been reported in patients treated with systemic metronidazole. Peripheral neuropathy has been reported with the post approval use of topical metronidazole. Immediate reevaluate METROGEL therapy if abnormal neurologic signs appear. (5.1)
- Blood Dyscrasias: METROGEL is a nitroimidazole; use with care in patients with evidence of, or history of, blood dyscrasia. (5.2)
- Contact Dermatitis: If dermatitis occurs, patients may need to discontinue use. (5.3)
- Eye Irritation: Topical metronidazole has been reported to cause tearing of the eyes. Avoid contact with the eyes. (5.4)

6 ADVERSE REACTIONS

Most common adverse reactions (incidence > 2%) are nasopharyngitis, upper respiratory tract infection, and headache. (6)

To report SUSPECTED ADVERSE REACTIONS, contact Galderma Laboratories, L.P. at 1-866-735-4137, or FDA at 1-800-FDA-1088 or www.fda.gov/medwatch

7 DRUG INTERACTIONS

Oral metronidazole has been reported to potentiate the anticoagulant effect of coumarin and warfarin, resulting in a prolongation of prothrombin time. Use caution when administering METROGEL concomitantly to patients who are receiving anticoagulant treatment. (7)

8 USE IN SPECIFIC POPULATIONS

- Lactation: Breastfeeding not recommended. (8.2)

FULL PRESCRIBING INFORMATION

1 INDICATIONS AND USAGE

METROGEL, 1% is indicated for the topical treatment of inflammatory lesions of rosacea.

2 DOSAGE AND ADMINISTRATION

- Cleanse treated areas before the application of METROGEL.
- Apply and rub in a thin film of METROGEL once daily to affected area(s).
- Cosmetics may be applied after the application of METROGEL.
- For topical use only, not for oral, ophthalmic, or intravaginal use.

3 DOSAGE FORMS AND STRENGTHS

Gel, 1%. METROGEL is a clear, colorless to pale yellow gel. Each gram of METROGEL contains 10 mg (1%) of metronidazole.

4 CONTRAINDICATIONS

METROGEL is contraindicated in patients with a history of hypersensitivity to metronidazole or to any other ingredient in the formulation.

5 WARNINGS AND PRECAUTIONS

5.1 Neurologic Disease

Peripheral neuropathy, characterized by numbness or paresthesia of an extremity, has been reported in patients treated with systemic metronidazole. Peripheral neuropathy has been reported with the post approval use of topical metronidazole. Immediately reevaluate METROGEL therapy if abnormal neurologic signs appear. Administer metronidazole with caution to patients with central nervous system diseases.

5.2 Blood Dyscrasias

METROGEL is a nitroimidazole; use with care in patients with evidence of, or history of, blood dyscrasia.

5.3 Contact Dermatitis

Irritant and allergic contact dermatitis have been reported with METROGEL. If dermatitis occurs, patients may need to discontinue use.

5.4 Eye Irritation

Topical metronidazole has been reported to cause tearing of the eyes. Avoid contact with the eyes.

6 ADVERSE REACTIONS

The following clinically significant adverse reactions are described elsewhere in the labeling:

- Neurologic Disease [see Warnings and Precautions (5.1)]
- Contact Dermatitis [see Warnings and Precautions (5.3)]
- Eye Irritation [see Warnings and Precautions (5.4)]

6.1 Clinical Trials Experience

Because clinical trials are conducted under widely varying conditions, adverse reaction rates observed in the clinical trials of a drug cannot be directly compared to rates in the clinical trials of another drug and may not reflect the rates observed in practice.
In a controlled clinical trial, 557 subjects used METROGEL and 189 subjects used the gel vehicle once daily for up to 10 weeks. The following table summarizes selected adverse reactions that occurred at a rate of ≥1% and at a higher rate than vehicle:

Table 1: Adverse Reactions That Occurred at a Rate of ≥1% and Higher Than Vehicle in Subjects Treated with METROGEL for Up to 10 Weeks
Preferred Term | METROGEL | Vehicle
 | (N= 557) N (%) | (N= 189) N (%)
Influenza | 8 (1.4) | 1 (0.5)
Upper respiratory tract infection | 14 (2.5) | 4 (2.1)
Urinary tract infection | 6 (1.1) | 1 (0.5)
Headache | 12 (2.2) | 1 (0.5)
Contact dermatitis | 7 (1.3) | 1 (0.5)
Hypertension | 6 (1.1) | 1 (0.5)

Table 2:Local Cutaneous Signs and Symptoms of Irritation That Were Worse Than Baseline in Subjects Treated with METROGEL for Up to 10 Weeks
 | METROGEL | Vehicle
Sign/Symptom | (N= 544) N (%) | (N= 184) N (%)
Dryness | 138 (25.4) | 63 (34.2)
Mild | 93 (17.1) | 41 (22.3)
Moderate | 42 (7.7) | 20 (10.9)
Severe | 3 (0.6) | 2 (1.1)
Scaling | 134 (24.6) | 60 (32.6)
Mild | 88 (16.2) | 32 (17.4)
Moderate | 43 (7.9) | 27 (14.7)
Severe | 3 (0.6) | 1 (0.5)
Pruritus | 86 (15.8) | 35 (19.0)
Mild | 53 (9.7) | 21 (11.4)
Moderate | 27 (5.0) | 13 (7.1)
Severe | 6 (1.1) | 1 (0.5)
Stinging/burning | 56 (10.3) | 28 (15.2)
Mild | 39 (7.2) | 18 (9.8)
Moderate | 7 (1.3) | 9 (4.9)
Severe | 10 (1.8) | 1 (0.5)

The following additional adverse reactions have been reported with the topical use of metronidazole: transient redness, metallic taste, tingling or numbness of extremities, and nausea.

6.2 Post Marketing Experience

The following adverse reaction has been identified during post-approval use of topical metronidazole. Because this reaction is reported voluntarily from a population of uncertain size, it is not always possible to reliably estimate the frequency or establish a causal relationship to drug exposure.
Nervous System Disorders: Peripheral neuropathy
Ophthalmic Adverse Reactions: Tearing of the eyes

7 DRUG INTERACTIONS

Oral metronidazole has been reported to potentiate the anticoagulant effect of coumarin and warfarin, resulting in a prolongation of prothrombin time. Use caution when prescribing for patients who are receiving anticoagulant treatment.

8 USE IN SPECIFIC POPULATIONS

8.1 Pregnancy

Risk Summary
Available data have not established an association between metronidazole use during pregnancy and major birth defects, miscarriage or other adverse maternal or fetal outcomes. No fetotoxicity was observed after oral administration of metronidazole in pregnant rats or mice. The available data do not allow the calculation of relevant comparisons between the systemic exposures of metronidazole observed in animal studies to the systemic exposures that would be expected in humans after topical use of METROGEL.
The background risk of major birth defects and miscarriage for the indicated population is unknown. All pregnancies have a background risk of birth defect, loss, or other adverse outcomes. In the U.S. general population, the estimated background risk of major birth defects and miscarriage in clinically recognized pregnancies is 2-4% and 15-20%, respectively.

8.2 Lactation

Risk Summary
It is not known whether metronidazole is present in human milk after topical administration. Published literature reports the presence of metronidazole in human milk after oral administration. There are no data on the effects of metronidazole on milk production. Because of the potential for serious adverse reactions, advise patients that breastfeeding is not recommended during treatment with METROGEL.

8.4 Pediatric Use

Safety and effectiveness of METROGEL have not been established in pediatric patients.

8.5 Geriatric Use

Sixty-six subjects aged 65 years and older were treated with METROGEL in the clinical study. No overall differences in safety or effectiveness were observed between these subjects and younger subjects, and other reported clinical experience has not identified differences in responses between the elderly and younger patients, but greater sensitivity of some older individuals cannot be ruled out.

11 DESCRIPTION

METROGEL (metronidazole) topical gel, 1% is a nitroimidazole for topical use. METROGEL is a clear, colorless to pale yellow, aqueous gel. Each gram contains 10 mg of metronidazole. Chemically, metronidazole is 2-methyl-5-nitro-1 Himidazole- 1-ethanol. The molecular formula for metronidazole is C6H9N3O3. It has the following structural formula:

Metronidazole has a molecular weight of 171.16. It is a white to pale yellow crystalline powder. It is slightly soluble in alcohol and has solubility in water of 10 mg/mL at 20°C. Metronidazole belongs to the nitroimidazole class of compounds.
The inactive ingredients are betadex, edetate disodium, hydroxyethyl cellulose, methylparaben, niacinamide, phenoxyethanol, propylene glycol, propylparaben and purified water.

12 CLINICAL PHARMACOLOGY

12.1 Mechanism of Action

The mechanism of action of metronidazole in the treatment of rosacea is unknown.

12.2 Pharmacodynamics

The pharmacodynamics of metronidazole in association with the treatment of rosacea are unknown.
Cardiac Electrophysiology: The effect of METROGEL on the QTc interval has not been adequately characterized.

12.3 Pharmacokinetics

Topical administration of a one-gram dose of METROGEL to the face of 13 subjects with moderate to severe rosacea once daily for 7 days resulted in a mean + SD Cmax of metronidazole of 32 + 9 ng/mL. The mean + SD AUC(0-24) was 595 + 154 ng*hr/mL. The mean Cmax and AUC(0-24) are less than 1% of the value reported for a single 250 mg oral dose of metronidazole. The time to maximum plasma concentration (Tmax) was 6-10 hours after topical application.

13 NONCLINICAL TOXICOLOGY

13.1 Carcinogenesis, Mutagenesis, Impairment of Fertility

Metronidazole has shown evidence of carcinogenic activity in studies involving chronic oral administration in mice and rats, but not in studies involving hamsters.
In several long-term studies in mice, oral doses of approximately 225 mg/m^2/day or greater were associated with an increase in pulmonary tumors and lymphomas. Several long-term oral studies in the rat have shown statistically significant increases in mammary and hepatic tumors at doses >885 mg/m^2/day.
Metronidazole has shown evidence of mutagenic activity in several in vitro bacterial assay systems. In addition, a dose-related increase in the frequency of micronuclei was observed in mice after intraperitoneal injections. An increase in chromosomal aberrations in peripheral blood lymphocytes was reported in patients with Crohn’s disease who were treated with 200 to 1200 mg/day of metronidazole for 1 to 24 months. However, in another study, no increase in chromosomal aberrations in circulating lymphocytes was observed in patients with Crohn’s disease treated with the drug for 8 months.

14 CLINICAL STUDIES

In a randomized, vehicle-controlled trial, 746 subjects with rosacea were treated with METROGEL or vehicle once daily for 10 weeks. Most subjects had a disease severity score of 3 (“moderate”) on the 5-point Investigator Global Assessment (IGA) scale, with 8 to 50 inflammatory lesions and no more than two nodules at baseline. The co-primary efficacy endpoints were the percent reduction in inflammatory lesion counts and percentage of subjects with success on IGA, defined as an IGA score of 0 (“clear”) or 1 (“almost clear”) at Week 10.
The efficacy results are shown in the following table:

Table 3: Inflammatory Lesion Counts and Global Scores in Subjects with Rosacea at Week 10 in a Clinical Trial
 | METROGEL |  | Vehicle
 | N | Results N (%) | N | Results N (%)
Inflammatory lesions | 557 |  | 189
Baseline, mean count |  | 18.3 |  | 18.4
Week-10, mean count |  | 8.9 |  | 12.8
Reduction |  | 9.4 (50.7) |  | 5.6 (32.6)
Investigator Global Assessment | 557 |  | 189
Subject clear or almost clear |  | 214 (38.42) |  | 52 (27.51)
Subject with no change |  | 159 (28.5) |  | 77 (40.7)

Subjects treated with METROGEL experienced a mean reduction of 9.4 inflammatory lesions in the Week-10 LOCF group, compared to a reduction of 5.6 for those treated with vehicle, or a difference in means of 3.8 lesions.

16 HOW SUPPLIED/STORAGE AND HANDLING

How Supplied
METROGEL®is clear, colorless to pale yellow in color, and supplied as follows:
60 gram tube – NDC 0299-3820-60

Storage and Handling
Store at controlled room temperature: 20° to 25°C (68° to 77°F), excursions permitted between 15° and 30°C (59° and 86°F).

17 PATIENT COUNSELING INFORMATION

Advise the patient to read the FDA-approved patient labeling (Patient Information).

Administration Instructions
Use as directed. Avoid contact with the eyes [see Warnings and Precautions (5.4)].
Cleanse treated areas before the application of METROGEL [see Dosage and Administration (2)]
Advise patients to report any adverse reaction to their healthcare providers.
Neurologic Disease
Advise patients to immediately report any abnormal neurologic signs to their healthcare provider [see Warnings and Precautions (5.1)].
Lactation
Advise women not to breastfeed during treatment with METROGEL [see Use in Specific Populations (8.2)].

Rx Only
US Patent No. 6,881,726 and 7,348,317

Marketed by:
Galderma Laboratories, L.P.
Dallas, TX 75201 USA
P5XXXX-X
Made in Canada
All trademarks are the property of their respective owners.

PATIENT INFORMATION

METROGEL® (MET-TRO-GEL)
(metronidazole)
Gel

Important: METROGEL is for use on the skin only (topical use). Do not use METROGEL in your mouth, eyes, or vagina.

What is METROGEL?
METROGEL is a prescription medicine used on the skin (topical) to treat pimples and bumps (inflammatory lesions) caused by a condition called rosacea.
It is not known if METROGEL is safe and effective in children.

Do not use METROGEL if you are allergic to metronidazole or any of the ingredients in METROGEL. See the end of this leaflet for a complete list of ingredients in METROGEL.

Before using METROGEL, tell your healthcare provider about all your medical conditions, including if you:

- have tingling or numbness in your hands or feet
- have or have had a blood disorder or disease
- are pregnant or plan to become pregnant. It is not known if METROGEL will harm your unborn baby
- are breastfeeding or plan to breastfeed. It is not known if METROGEL passes into your breast milk. Do not breastfeed during treatment with METROGEL. Talk to your healthcare provider about the best way to feed your baby during treatment with METROGEL.

Tell your healthcare provider about all of the medicines you take, including prescription and over-the-counter medicines, vitamins, and herbal supplements.
Know the medicines you take. Keep a list of them to show your healthcare provider and pharmacist when you get a new medicine.

How should I use METROGEL?

- Use METROGEL exactly as your healthcare provider tells you to.
- Cleanse the treated area before applying METROGEL.
- Apply and rub in a thin film of METROGEL 1 time a day to the affected area(s).
- You can apply cosmetics after applying METROGEL.
- Avoid contact of METROGEL with your eyes.

What are the possible side effects of METROGEL?
METROGEL may cause serious side effects, including:

- Peripheral neuropathy. Tingling, burning, pain or numbness in the hands or feet (peripheral neuropathy) have happened in people treated with metronidazole used on the skin. Tell your healthcare provider if you experience tingling, burning, pain or numbness in your hands or feet during treatment with METROGEL.
- Skin reactions, including allergic reactions. Tell your healthcare provider if you develop any skin reactions, including rash, itching, redness, swelling, or blisters during treatment with METROGEL.
- Eye irritation. Tearing from eye irritation has happened in people treated with metronidazole used on the skin. Tell your healthcare provider if you experience tearing, redness or discomfort of the eyes during treatment with METROGEL.

The most common side effects of METROGEL include:

- sore throat and nasal congestion
- upper respiratory tract infections
- headache

Tell your healthcare provider if you get any side effects during treatment with METROGEL.

These are not all of the possible side effects of METROGEL.
Call your doctor for medical advice about side effects. You may report side effects to FDA at 1-800-FDA-1088.
You may also report side effects to Galderma Laboratories, L.P. at 1-866-735-4137.

How should I store METROGEL?

- Store METROGEL at room temperature between 68°F to 77°F (20°C to 25°C).

Keep METROGEL and all medicines out of the reach of children.

General information about the safe and effective use of METROGEL.
Medicines are sometimes prescribed for purposes other than those listed in a Patient Information leaflet. Do not use METROGEL for a condition for which it was not prescribed. Do not give METROGEL to other people, even if they have the same symptoms that you have. It may harm them. You can ask your pharmacist or healthcare provider for information about METROGEL that is written for health professionals.

What are the ingredients in METROGEL?
Active ingredient: metronidazole
Inactive ingredients: betadex, edetate disodium, hydroxyethyl cellulose, methylparaben, niacinamide, phenoxyethanol, propylene glycol, propylparaben and purified water
Marketed by: Galderma Laboratories, Dallas, Texas 75201 USA
P5XXXX-X
Made in Canada
US Patent No. 6,881,726 and 7,348,317
For more information, call 1-866-735-4137.
This Patient Information has been approved by the U.S. Food and Drug Administration.
Issued: 11/2023

PACKAGE LABEL - 60g Tube

metrogel 1%
(metronidazole) Gel 1%
For topical use only
NDC 0299-3820-60
Rx Only
NET WT. 60 g
For topical use only.
Not for oral, ophthalmic or intravaginal use.
Store at controlled room temperature, 68° to 77°F (20° - 25°C), excursions permitted between 59° to 86°F (15° - 30°C).
Keep out of reach of children.
Usual dosage: Apply a thin film once a day to the affected areas. See package insert for complete prescribing instructions.
Each gram contains: 10 mg (1%) metronidazole as active ingredient in a gel base consisting of betadex, edetate disodium, hydroxyethl cellulose, methylparaben, niacinamide, phenoxyethanol, propylene glycol, propylparben, and purified water.

Marketed by:
GALDERMA LABORATORIES, L.P.
Fort Worth, TX 76177 USA
All trademarks are the property of their respective owners.
Made in Canada.
P50741-6